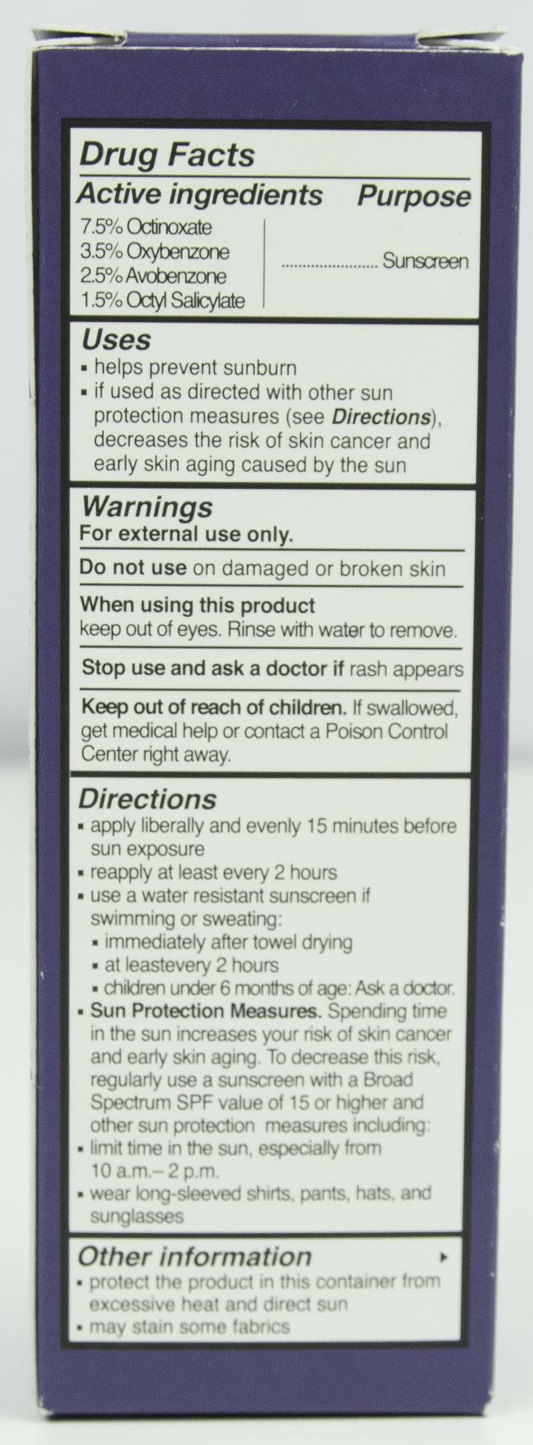 DRUG LABEL: SLMD Moisturizer with SPF
NDC: 59958-403 | Form: LOTION
Manufacturer: Owen Biosciences, Inc.
Category: otc | Type: HUMAN OTC DRUG LABEL
Date: 20230116

ACTIVE INGREDIENTS: OCTINOXATE 7.5 g/100 g; OXYBENZONE 3.5 g/100 g; AVOBENZONE 2.5 g/100 g; OCTISALATE 1.5 g/100 g
INACTIVE INGREDIENTS: WATER 60.628 g/100 g; CETYL ALCOHOL 2.5 g/100 g; GLYCERIN 2 g/100 g; CETYL PHOSPHATE 2 g/100 g; DIMETHICONE 2 g/100 g; BEHENTRIMONIUM METHOSULFATE 1 g/100 g

SLMD Moisturizer with SPF

Active Ingredients

Octinoxate 7.50%
Oxybenzone 3.50%
Avobenzone 2.50%
Octisalate 1.50%

Uses

- helps prevent sunburn
- if used as directed with other sun protection measures (see Directions), decreases the risk of skin cancer and early skin aging caused by the sun

Warnings For external use only

Do not use on damaged or broken skin

When using this product

keep out of eyes. Rinse with water to remove.

skin irritation and dryness is more likely to occur if you use another topical acne medication at the same time. If irritation occurs, only use one topical acne medication at a time.

Keep out of reach of children.

If swallowed, get medical help or contact a Poison Control Center right away.

Directions

- apply liberally and evenly 15 minutes before sun exposure
- reapply at least every 2 hours
- use a water resistant sunscreen if swimming or sweating:
- immediately after towel drying
- at least every two hours
- children under 6 months of age: ask a doctor
- Sun Protection Measures. Spending time in the sun increases your risk of skin cancer and early skin aging. To decrease thsi risk, regularly use a sunscreen with a Broad Spectrum SPF value of 15 or higher and other sun protection measures including:
- limit time in the sun, especially from 10 a.m. - 2 p.m.
- wear long sleeved shirts, pants, hats and sunglasses

PURPOSE

sunscreen

DOSAGE AND ADMINISTRATION

topical sunscreen

Other information

- protect this product in this containerfrom excessive heat and direct sun
- may stain some fabrics

Inactive ingredients

Water
Emulsifying Wax NF
Cetyl Alcohol
Glycerin
DEA-Cetyl Phosphate
Dimethicone
Behentrimonium Methosulfate
Cetearyl Alcohol
Myristoyl Pentapeptide-17
Myristoyl Tetrapeptide-13
Ascorbyl Linoleate
Retinyl Linoleate
Lysophosphatidic acid
Panthenol
Allantoin
Arginine
Beta-Glucan
Sodium Carboxymethyl Beta-Glucan
Ethyl Macadamiate
Borago Officinalis Seed Oil
Triticum Vulgare (Wheat) Germ Oil
Tocopheryl Acetate
Retinyl Palmitate
Citrus Paradisi (Grapefruit) Fruit Extract
Camellia Sinensis Leaf Extract
Rosa Canina Fruit Extract
Hamamelis Virginiana (Witch Hazel) Extract
Polyglyceryl-3 Polyricinoleate
Polyglyceryl 5 Oleate
PPG-2 Myristyl Ether Propionate
Pentaerythrityl Tetracaprylate/Tetracaprate
Disodium EDTA
Caprylyl Glycol
Phenoxyethanol

Do not use

- on damaged or broken skin

Stop us and ask a doctor if

irritation becomes severe

Daily Moisturizer Back.jpg